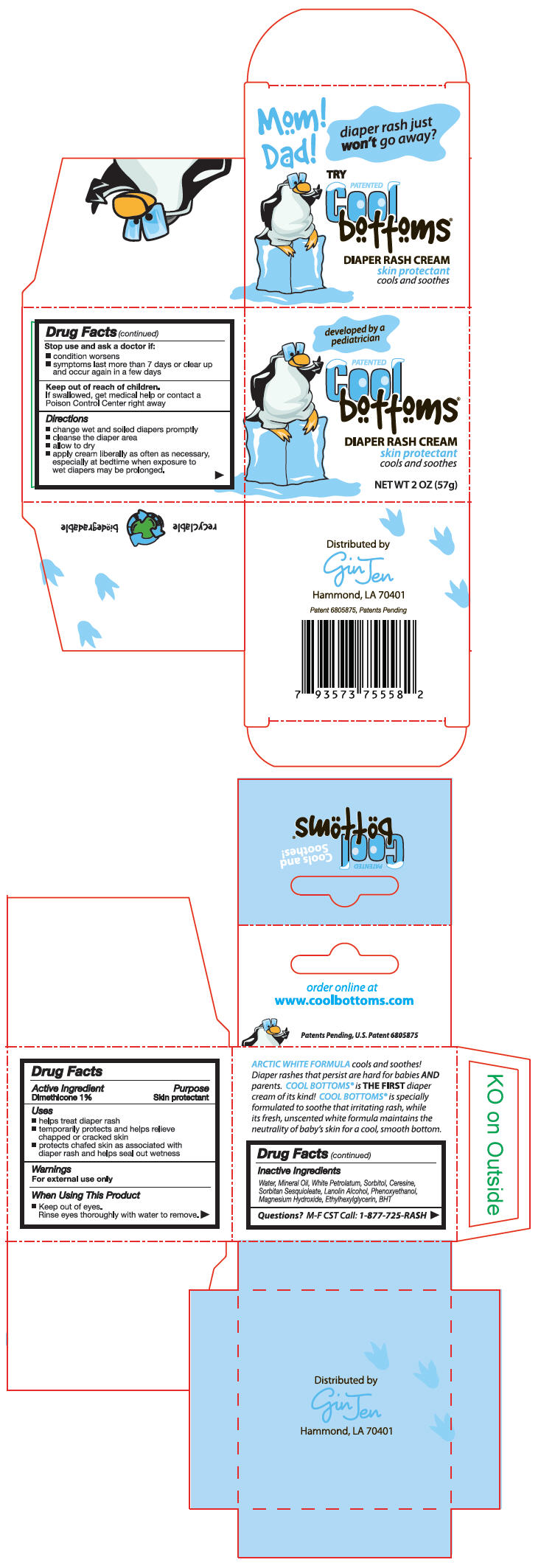 DRUG LABEL: Coolbottoms 
NDC: 50952-001 | Form: CREAM
Manufacturer: pH R&D LLC
Category: otc | Type: HUMAN OTC DRUG LABEL
Date: 20101119

ACTIVE INGREDIENTS: Dimethicone 0.57 g/57 g
INACTIVE INGREDIENTS: Water; Mineral Oil; Petrolatum; Sorbitol; Sorbitan Sesquioleate; Lanolin Alcohols; Phenoxyethanol; Magnesium Hydroxide; Ethylhexylglycerin; Butylated Hydroxytoluene

Cool
bottoms®
DIAPER RASH CREAM

Drug Facts

Active Ingredient

Dimethicone 1%

Purpose

Skin protectant

Uses

- helps treat diaper rash
- temporarily protects and helps relieve chapped or cracked skin
- protects chafed skin as associated with diaper rash and helps seal out wetness

Warnings

For external use only

When Using This Product

- Keep out of eyes.
  Rinse eyes thoroughly with water to remove.

Stop use and ask a doctor if:

- condition worsens
- symptoms last more than 7 days or clear up and occur again in a few days

Keep out of reach of children.

If swallowed, get medical help or contact a Poison Control Center right away

Directions

- change wet and soiled diapers promptly
- cleanse the diaper area
- allow to dry
- apply cream liberally as often as necessary, especially at bedtime when exposure to wet diapers may be prolonged.

Inactive Ingredients

Water, Mineral Oil, White Petrolatum, Sorbitol, Ceresine, Sorbitan Sesquioleate, Lanolin Alcohol, Phenoxyethanol, Magnesium Hydroxide, Ethylhexylglycerin, BHT

Questions?

M-F CST Call: 1-877-725-RASH

Distributed by
GinJen
Hammond, LA 70401

PRINCIPAL DISPLAY PANEL - 57g jar carton

developed by a
pediatrician

PATENTED
Cool
bottoms®
DIAPER RASH CREAM
skin protectant
cools and soothes

NET WT 2 OZ (57g)